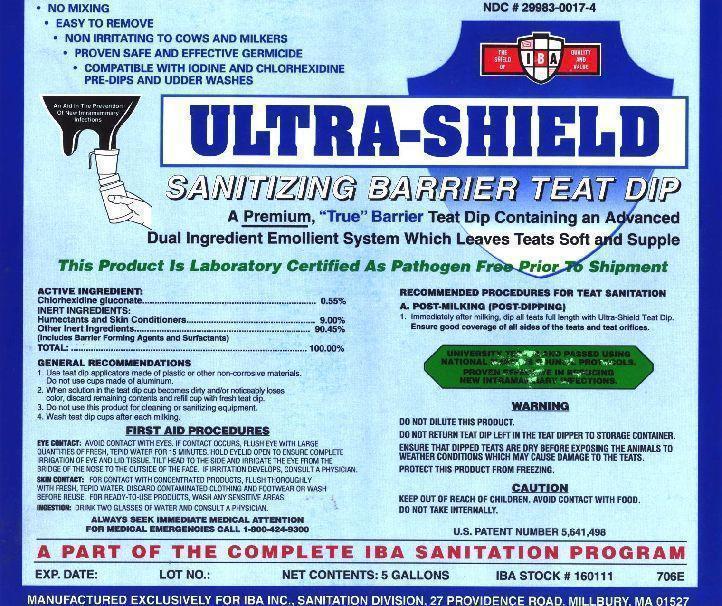 DRUG LABEL: ULTRA-SHIELD
NDC: 29983-0017 | Form: SOLUTION
Manufacturer: IBA
Category: animal | Type: OTC ANIMAL DRUG LABEL
Date: 20241231

ACTIVE INGREDIENTS: CHLORHEXIDINE GLUCONATE 2.75 g/1 L
INACTIVE INGREDIENTS: WATER

ULTRA-SHIELD SANITIZING BARRIER TEAT DIP A PREMIUM, "TRUE" BARRIER TEAT DIP CONTAINING AN ADVANCED DUEL INGREDIENT EMOLLIENT SYSTEM WHICH LEAVES TEATS SOFT AND SUPPLE.
PRODUCT IS LABORATORY CERTIFIED AS PATHOGEN FREE PRIOR TO SHIPMENT

ACTIVE INGREDIENT

Chlorhexidine gluconate............ 0.55%

INERT INGREDIENTS:
Humectants and Skin Conditioners.................................9.00%
Other inert ingredients....................................................90.45%
(Including Surfactants and Barrier Forming Agents)
TOTAL.............................................................................100.00%

INDICATIONS AND USAGE

GENERAL RECOMMENDATIONS
1. Use teat dip applicators made of plastic or other non-corrosive materials. Do not use cups made of aluminum.
2. When solution in the teat dip cup becomes dirty and/or noticeably loses color, discard remaining contents and refill cup with fresh teat dip.
3. Do not use this product for cleaning or sanitizing equipment
4. Wash Teat Dip cups after each milking.

A. POST-MILKING (POST DIPPING)
Immediately after milking dip all teats full length with ULTRA-SHIELD Teat Dip Ensure good coverage of all sides of the teats and teat orifices.

UNIVERSITY TESTED AND PASSED USING NATIONAL MASTITIS COUNCIL PROTOCOLS.

Ã‚Â Ã‚Â Ã‚Â Ã‚Â Ã‚Â Ã‚Â Ã‚Â PROVEN EFFECTIVE IN REDUCING NEW INTRAMAMMARY INFECTIONS.

PART OF THE COMPLETE IBA SANITATION PROGRAM

WARNING

DO NOT DILUTE THIS PRODUCT
DO NOT RETURN TEAT DIP LEFT IN THE TEAT DIPPER TO STORAGE CONTAINER
ENSURE THAT DIPPED TEATS ARE DRY BEFORE EXPOSING THE ANIMALS TO WEATHER CONDITIONS WHICH MAY CAUSE DAMAGE TO THE TEATS.
PROTECT THIS PRODUCT FROM FREEZING.

FIRST AID PROCEDURES

EYE CONTACT: IMMEDIATELY FLUSH EYE WITH LARGE AMOUNTS OF FRESH, TEPID WATER FOR 15 MINUTES. HOLD EYELID OPEN TO ENSURE COMPLETE IRRIGATION OF EYE AND LID TISSUES . TILT HEAD TO THE SIDE AND IRRIGATE THE EYE FROM THE BRIDGE OF THE NOSE TO THE OUTSIDE OF THE FACE.

SKIN CONTACT: FOR CONTACT WITH CONCENTRATED PRODUCTS, FLUSH THOROUGHLY WITH FRESH,TEPID WATER, DISCARD CONTAMINATED CLOTHING AND FOOTWEAR OR WASH BEFORE REUSE. FOR READY-TO-USE PRODUCTS, WASH ANY SENSITIVE AREAS.

INGESTION: DO NOT INDUCE VOMITING. NEVER GIVE ANYTHING BY MOUTH TO AN UNCONSCIOUS PERSON. DRINK LARGE AMOUNTS OF WATER. IF VOMITING OCCURS KEEP AIRWAYS OPEN. KEEP HEAD LOWER THAN THE HIPS TO PREVENT ASPIRATION INTO THE LUNGS.

ALWAYS SEEK IMMEDIATE MEDICAL ATTENTION

FOR MEDICAL EMERGENCIES CALL 1-800-424-9300